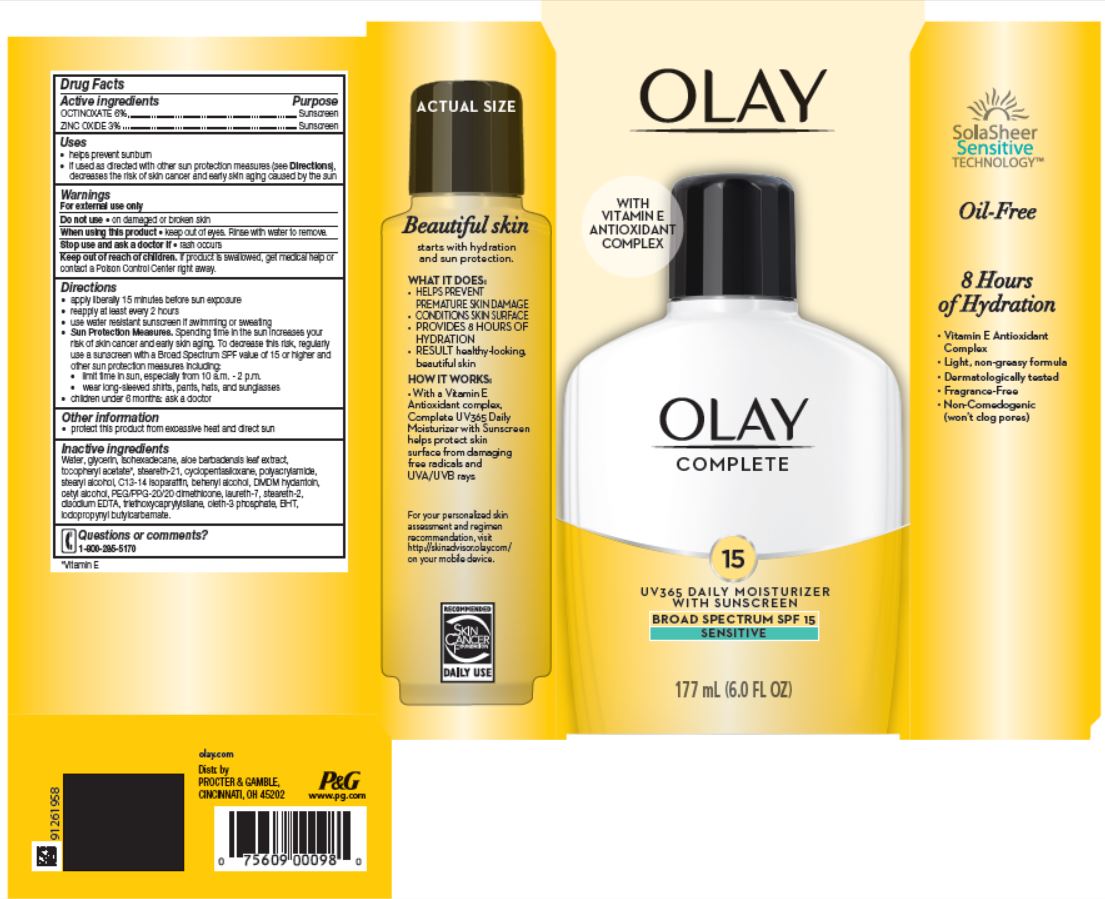 DRUG LABEL: Olay Complete UV365 Daily Moisturizer Sensitive
NDC: 69423-194 | Form: LOTION
Manufacturer: The Procter & Gamble Manufacturing Company
Category: otc | Type: HUMAN OTC DRUG LABEL
Date: 20251124

ACTIVE INGREDIENTS: ZINC OXIDE 3 g/100 mL; OCTINOXATE 6 g/100 mL
INACTIVE INGREDIENTS: BUTYLATED HYDROXYTOLUENE; WATER; GLYCERIN; ISOHEXADECANE; .ALPHA.-TOCOPHEROL ACETATE; ALOE VERA LEAF; STEARETH-21; CYCLOMETHICONE 5; STEARYL ALCOHOL; DOCOSANOL; C13-14 ISOPARAFFIN; DMDM HYDANTOIN; CETYL ALCOHOL; PEG/PPG-20/20 DIMETHICONE; STEARETH-2; EDETATE DISODIUM; LAURETH-7; TRIETHOXYCAPRYLYLSILANE; OLETH-3 PHOSPHATE; IODOPROPYNYL BUTYLCARBAMATE

Olay® Complete UV365 Daily Moisturizer Sensitive
Broad Spectrum SPF 15

Drug Facts

ACTIVE INGREDIENT

Active ingredients | Purpose
Octinoxate 6% | Sunscreen
Zinc Oxide 3% | Sunscreen

Uses

- helps prevent sunburn
- if used as directed with other sun protection measures (see Directions), decreases the risk of skin cancer and early skin aging caused by the sun

Warnings

For external use only

Do not use

- on damaged or broken skin

When using this product

- keep out of eyes. Rinse with water to remove.

Stop use and ask a doctor if

- rash occurs

Keep out of reach of children. If product is swallowed, get medical help or contact a Poison Control Center right away.

Directions

- apply liberally 15 minutes before sun exposure
- reapply at least every 2 hours
- use water resistant sunscreen if swimming or sweating
- Sun Protection Measures. Spending time in the sun increases your risk of skin cancer and early skin aging. To decrease this risk, regularly use a sunscreen with a Broad Spectrum SPF value of 15 or higher and other sun protection measures including:
  - limit time in sun, especially from 10 a.m. – 2 p.m.
  - wear long-sleeved shirts, pants, hats, and sunglasses
- children under 6 months: ask a doctor

Other information

- protect this product from excessive heat and direct sun

Inactive ingredients

water, glycerin, isohexadecane, aloe barbadensis leaf extract, tocopheryl acetate, steareth-21, cyclopentasiloxane, polyacrylamide, stearyl alcohol, C13-14 isoparaffin, behenyl alcohol, DMDM hydantoin, cetyl alcohol, PEG/PPG-20/20 dimethicone, laureth-7, steareth-2, disodium EDTA, triethoxycaprylylsilane, oleth-3 phosphate, BHT, iodopropynyl butylcarbamate.

Questions or comments?

Call 1-800-285-5170

Distr. by PROCTER & GAMBLE,
CINCINNATI, OH 45202

PRINCIPAL DISPLAY PANEL - 177 mL Bottle Carton

OLAY®

COMPLETE

15

UV365 Daily Moisturizer

with Sunscreen

BROAD SPECTRUM SPF 15
SENSITIVE

177 mL (6.0 FL OZ)